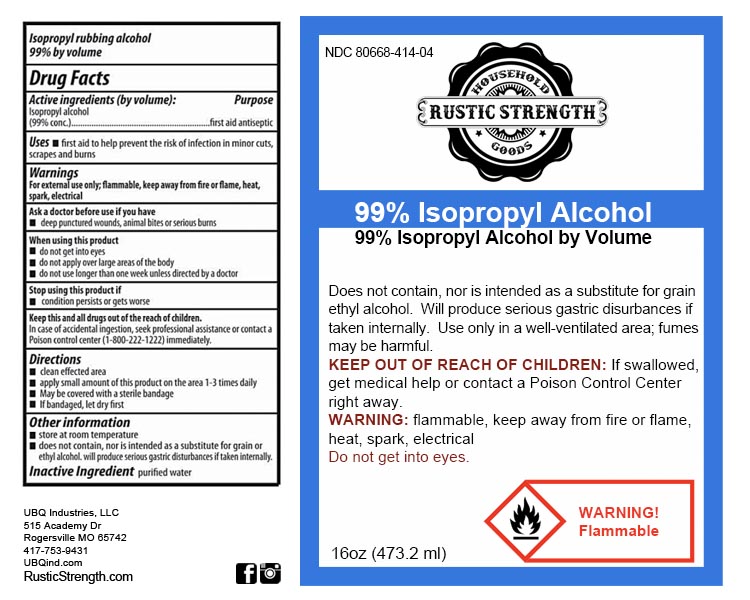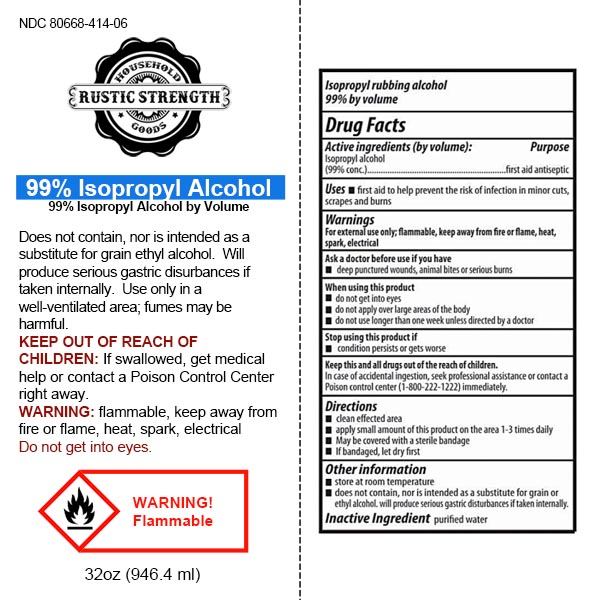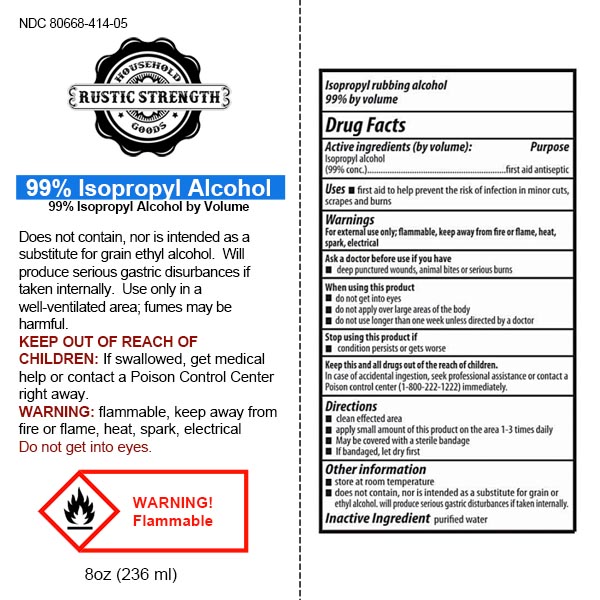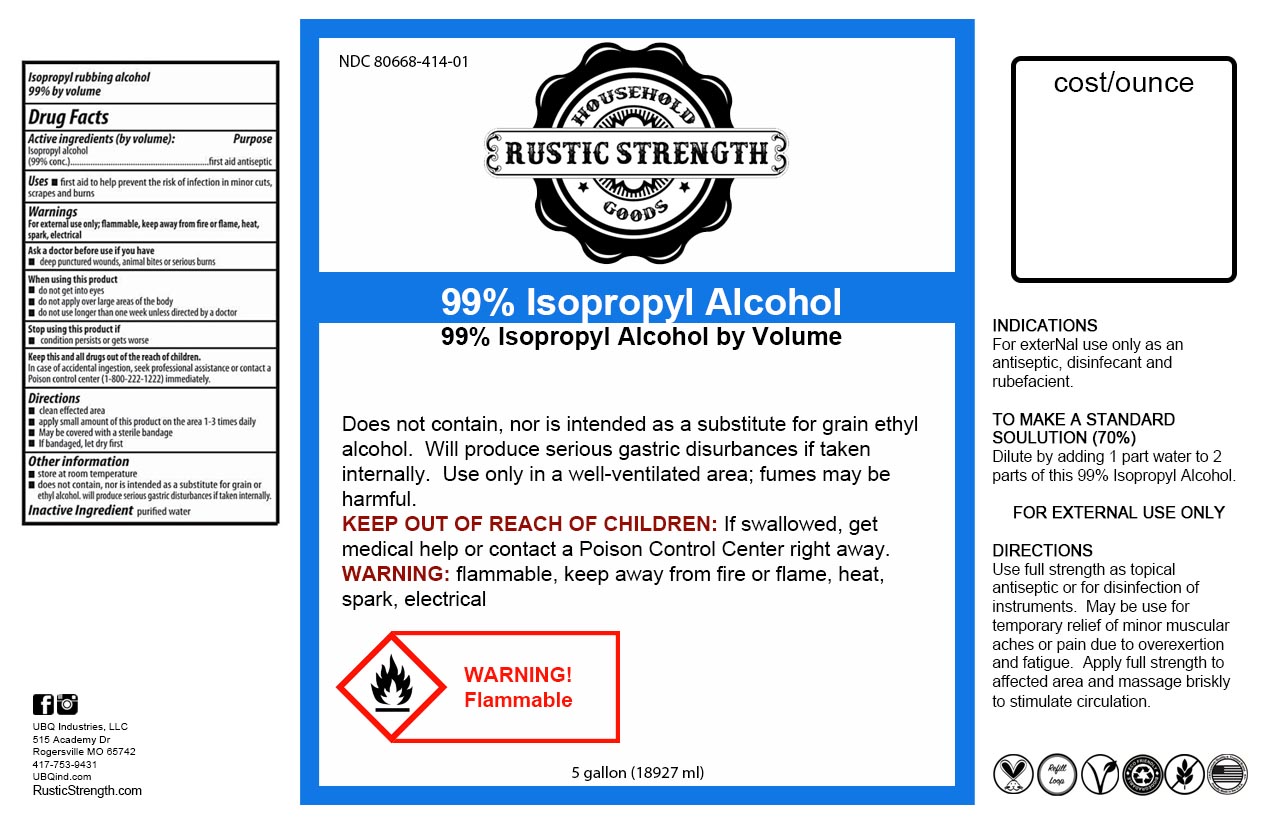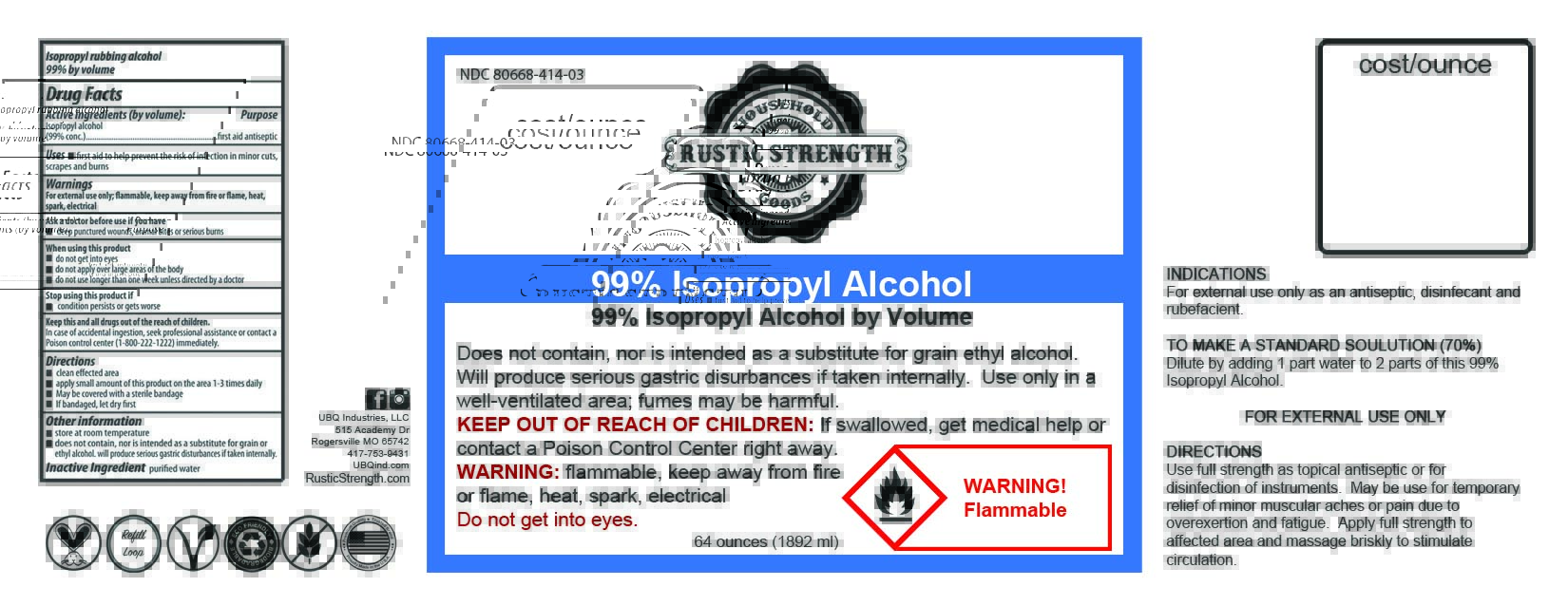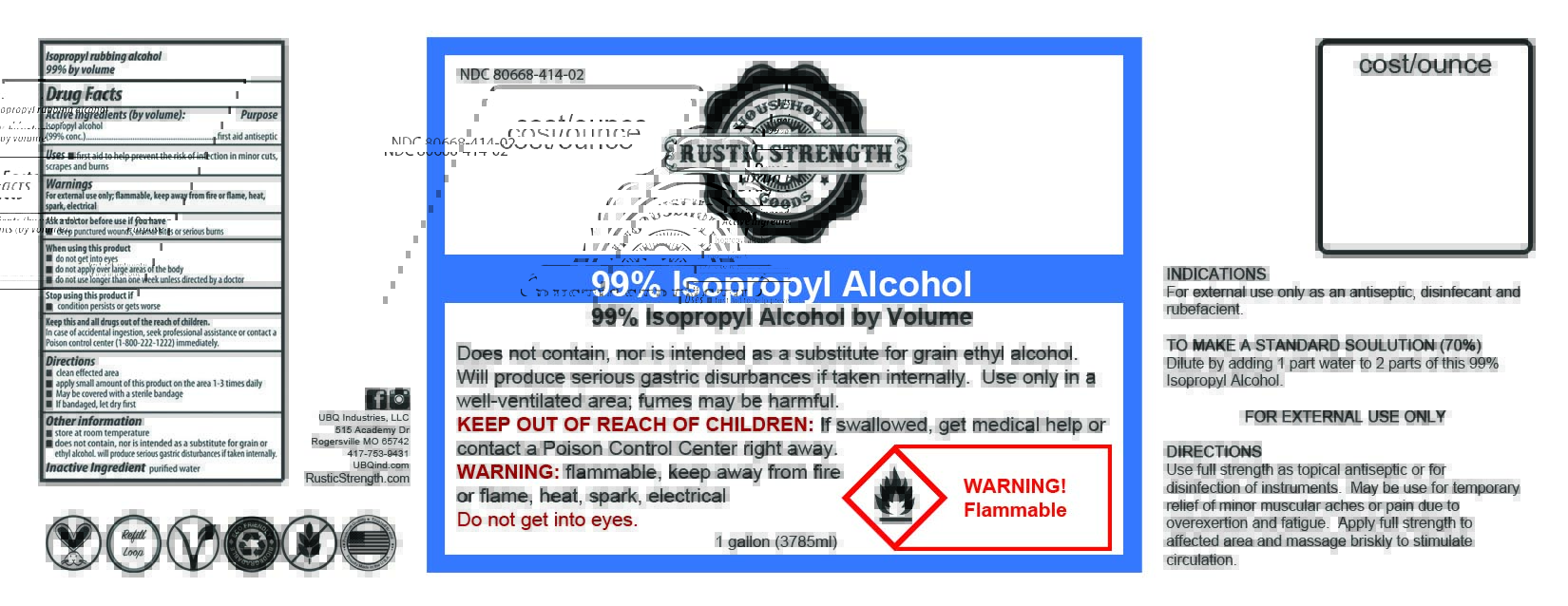 DRUG LABEL: Isopropyl Alcohol 99%
NDC: 80668-414 | Form: LIQUID
Manufacturer: UBQ Industries, LLC
Category: otc | Type: HUMAN OTC DRUG LABEL
Date: 20211123

ACTIVE INGREDIENTS: ISOPROPYL ALCOHOL 99 mL/100 mL
INACTIVE INGREDIENTS: WATER 1 mL/100 mL

Isopropyl Alcohol 99%

Active Ingredient(s)

Isopropyl Alcohol 99% v/v. Purpose: Antiseptic

Purpose Section

first aid antiseptic, isopropyl alcohol

Indications and usage section

first aid to help prevent the risk of infection in minor cuts, scrapes and burns

Warnings Section

For external use only. Flammable. Keep away from heat or flame

Ask a doctor before use if you have

deep puncture wounds, animal bites or serious burns

When using this product

do not get into eyes, do not apply over large areas of the body, do not use longer than one week unless directed by a doctor

Stop using this product if

condition persists or gets worse

Keep this and all drugs our of the reach of children

In case of accidentail ingestion, seek professional assistance or contact a Poison Control Center (1-800-222-1222) immediately

Directions

clean effected area. apply small amount of this product on the area 1 - 3 times daily, may be covered with a sterile bandage, if bandaged, let dry first

Other information

store at room temperature. does not contain, nor is intended as a substitute for grain or ethyl alcohol. will produce serious gastric disturbances if taken internally

Inactive Ingredients

purified water

Package Label - Principal Display Panel

236 ml NDC 80668-414-05

946.4 ml NDC 80668-414-06

18927 ml NDC 80668-414-01

3785 ml NDC 80668-414-02

1892 ml NDC 80668-414-03

473.2ml NDC 80668-414-04